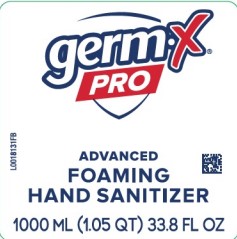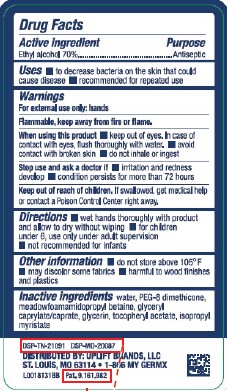 DRUG LABEL: Hand Sanitizer
NDC: 83986-456 | Form: GEL
Manufacturer: UpLift Brands, LLC
Category: otc | Type: HUMAN OTC DRUG LABEL
Date: 20260115

ACTIVE INGREDIENTS: ALCOHOL 70 mL/100 mL
INACTIVE INGREDIENTS: WATER; PEG-8 DIMETHICONE; MEADOWFOAMAMIDOPROPYL BETAINE; GLYCERYL CAPRYLATE/CAPRATE; GLYCERIN; .ALPHA.-TOCOPHEROL ACETATE; ISOPROPYL MYRISTATE

Germ-X 456.001/456AC
70% Alcohol Foaming Hand Sanitizer

Active ingredient

Ethyl alcohol 70%

Purpose

Antiseptic

Use

- to decrease bacteria on the skin that could cause disease
- recommended for repeated use

Warnings

For external use only: hands

Flammable. Keep away from fire or flame.

When using this product

- keep out of eyes. In case of contact with eyes, flush thoroughly with water.
- avoid contact with broken skin
- do not inhale or ingest

Stop use and ask a doctor if

- irritation or redness develops
- condition persists for more than 72 hours

Keep out of reach children

If swallowed, get medical help or contact a Poison Control Center right away.

Directions

- wet hands thoroughly with product and allow to dry without wiping
- for children under 6, use only under adult suervision
- not recommended for infants

Other information

- do not store above 105° F
- may discolor some fabrics
- harmful to wood finishes and plastics

Inactive ingredients

water, PEG-8 Dimethicone, meadowfoamamidopropyl betaine, glyceryl caprylate/caprate, glycerin, tocopheryl acetate, isopropyl myristate

Adverse reaction

DSP-TN-21091 DSP-MO-20087

Pat. 9,161,982

DISTRIBUTED BY: UPLIFT BRANDS, LLC

ST. LOUIS, MO 63114

1-866 MY GERMX

Principal display panel

germ-x®

PRO

ADVANCED

FOAMING HAND SANITIZER

1000 mL (1.05 QT) 33.8 FL OZ